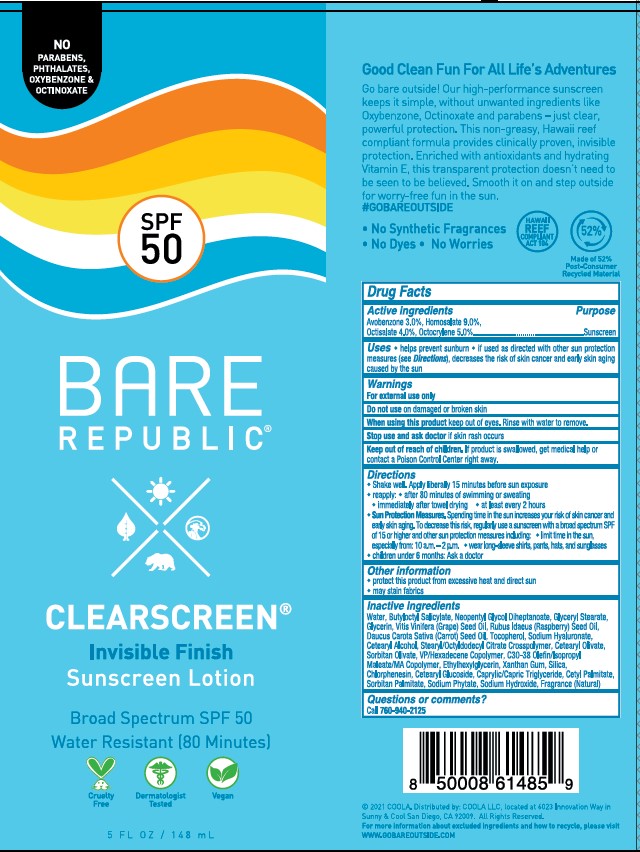 DRUG LABEL: COOLA BARE REPUBLIC CLEARSCREEN SPF50
NDC: 79753-014 | Form: LOTION
Manufacturer: COOLA, LLC
Category: otc | Type: HUMAN OTC DRUG LABEL
Date: 20251215

ACTIVE INGREDIENTS: HOMOSALATE 90 mg/1 mL; AVOBENZONE 30 mg/1 mL; OCTOCRYLENE 50 mg/1 mL; OCTISALATE 40 mg/1 mL
INACTIVE INGREDIENTS: CETYL PALMITATE; WATER; NEOPENTYL GLYCOL DIHEPTANOATE; CETYL ALCOHOL; RASPBERRY SEED OIL; CETEARYL GLUCOSIDE; CETEARYL OLIVATE; BENZYL ALCOHOL; CHLORPHENESIN; VINYLPYRROLIDONE/HEXADECENE COPOLYMER; SILICON DIOXIDE; HYALURONATE SODIUM; CARROT SEED OIL; GLYCERYL 1-STEARATE; XANTHAN GUM; SORBITAN OLIVATE; .ALPHA.-TOCOPHEROL, DL-; GRAPE SEED OIL; SODIUM HYDROXIDE; PHYTATE SODIUM; ARACHIDYL ALCOHOL; GLYCERIN; STEARYL/OCTYLDODECYL CITRATE CROSSPOLYMER; BUTYLOCTYL SALICYLATE; MEDIUM-CHAIN TRIGLYCERIDES; ETHYLHEXYLGLYCERIN; SORBITAN MONOPALMITATE

COOLA BARE REPUBLIC CLEARSCREEN SPF50 LOTION

Active ingredients

Avobenzone 3.0%

Homosalate 9.0%

Octisalate 4.0%

Octocrylene 5.0%

Purpose

Sunscreen

Uses

- helps prevent sunburn
- if used as directed with other sun protection measures (see Directions), decreases the risk of skin cancer and early skin aging caused by the sun

Warnings

For external use only

Do not use

- on damaged or broken skin.

When using this product

- keep out of eyes. Rinse with water to remove.

Stop use and ask a doctor if

- rash occurs.

Keep out of the reach of children

If swallowed, get medical help or contact a Poison Control Center right away.

Directions

- apply liberally 15 minutes before sun exposure

- reapply:

-after 80 minutes of swimming or sweating

-immediately after towel drying

-at least every 2 hours

- children under 6 months of age: Ask a doctor
- Sun Protection Measures. Spending time in the sun increases your risk of skin cancer and early skin aging. To decrease this risk, regularly use a sunscreen with a Broad Spectrum SPF value of 15 or higher and other sun protection measures including:

-limit time in the sun, especially from 10 a.m.-2 p.m.

-wear long-sleeved shirts, pants, hats, and sunglasses

Other information

- protect this product from excessive heat and direct sun
- may stain or damage some fabrics, materials or surfaces

Inactive Ingredients

Behenyl Alcohol, Butyloctyl Salicylate, C30-38 Olefin/Isopropyl Maleate/MA Copolymer, Caprylic/Capric Triglyceride, Cetearyl Alcohol, Cetearyl Gluoside, Cetearyl Olivate, Cetyl Palmitate, Chlorophenesin, Daucus Carota Sativa (Carrot) Seed Oil, Ethylhexylglycerin, Fragrance, Glycerin, Glyceryl Caprylate, Glyceryl Stearate, Neopentyl Glycol Diheptanoate, Rubus Idaeus (Raspberry) Seed Oil, Silica, Sodium Hyaluronate, Sodium Hydroxide, Sodium Phytate, Sorbitan Olivate, Sorbitan Palmitate, Stearyl/Octyldodecyl Citrate Crosspolymer, Tocopheryl (Vitamin E), Vitis Vinifera (Grape) Seed Oil, VP/Hexadecene Copolymer, Water, Xanthan Gum